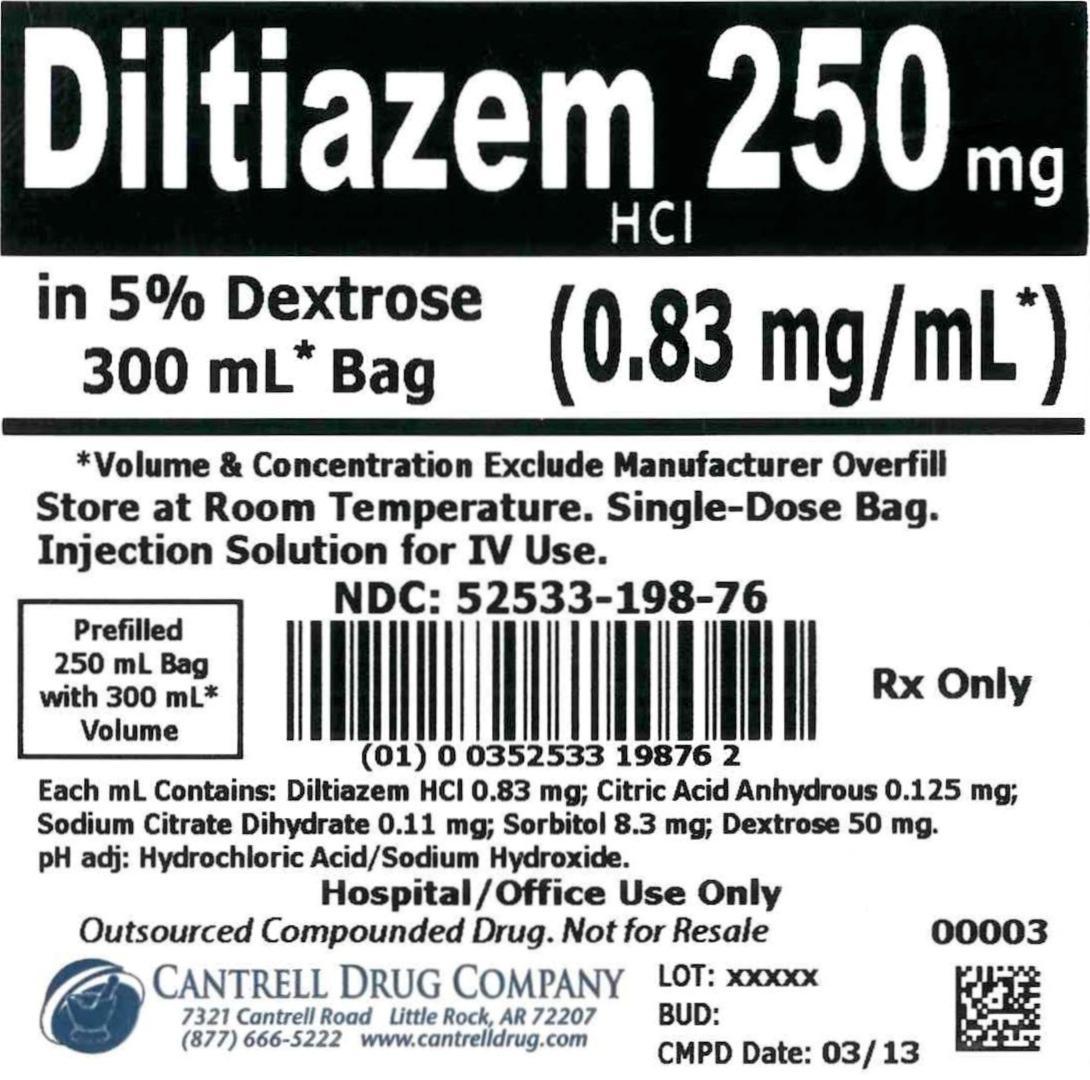 DRUG LABEL: Diltiazem HCl
NDC: 52533-198 | Form: INJECTION, SOLUTION
Manufacturer: Cantrell Drug Company
Category: prescription | Type: HUMAN PRESCRIPTION DRUG LABEL
Date: 20150112

ACTIVE INGREDIENTS: DILTIAZEM HYDROCHLORIDE 0.83 mg/1 mL
INACTIVE INGREDIENTS: DEXTROSE 50 mg/1 mL; ANHYDROUS CITRIC ACID 0.125 mg/1 mL; TRISODIUM CITRATE DIHYDRATE 0.11 mg/1 mL; SORBITOL 8.3 mg/1 mL; WATER

Diltiazem HCl 250 mg in 5% Dextrose 300 mL Bag